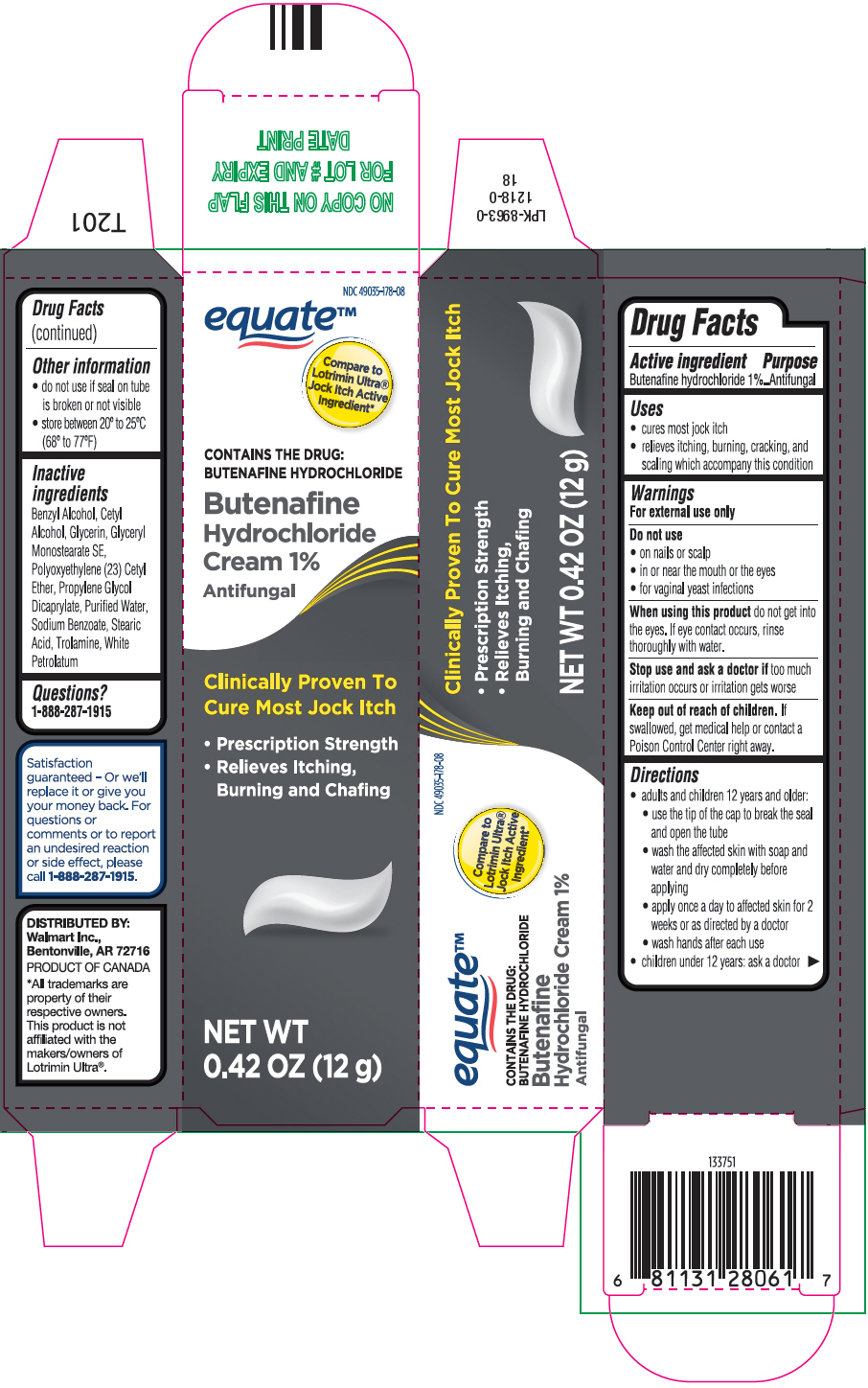 DRUG LABEL: Butenafine Hydrochloride 

NDC: 49035-178 | Form: CREAM
Manufacturer: Wal-Mart Stores Inc
Category: otc | Type: HUMAN OTC DRUG LABEL
Date: 20250703

ACTIVE INGREDIENTS: BUTENAFINE HYDROCHLORIDE 10 mg/1 g
INACTIVE INGREDIENTS: BENZYL ALCOHOL; CETYL ALCOHOL; GLYCERIN; GLYCERYL STEARATE SE; CETETH-23; PROPYLENE GLYCOL DICAPRYLATE; WATER; SODIUM BENZOATE; STEARIC ACID; TROLAMINE; PETROLATUM

Butenafine Hydrochloride Cream 1%
Jock Itch

Drug Facts

Active ingredient

Butenafine hydrochloride 1%

Purpose

Antifungal

Uses

- cures most jock itch
- relieves itching, burning, cracking, and scaling which accompany this condition

Warnings

For external use only

Do not use

- on nails or scalp
- in or near the mouth or the eyes
- for vaginal yeast infections

WHEN USING

When using this productdo not get into the eyes. If eye contact occurs, rinse thoroughly with water.

Stop use and ask a doctor iftoo much irritation occurs or irritation gets worse

Keep out of reach of children.If swallowed, get medical help or contact a Poison Control Center right away.

Directions

- adults and children 12 years and older:
  - use the tip of the cap to break the seal and open the tube
  - wash the affected skin with soap and water and dry completely before applying
  - apply once a day to affected skin for 2 weeks or as directed by a doctor
  - wash hands after each use
- children under 12 years: ask a doctor

Other information

- do not use if seal on tube is broken or not visible
- store between 20° to 25° C (68° to 77° F)

Inactive ingredients

Benzyl Alcohol, Cetyl Alcohol, Glycerin, Glyceryl Monostearate SE, Polyoxyethylene (23) Cetyl Ether, Propylene Glycol Dicaprylate, Purified Water, Sodium Benzoate, Stearic Acid, Trolamine, White Petrolatum

Questions?

1-888-287-1915

DISTRIBUTED BY:
Walmart Inc.,
Bentonville, AR 72716

PRINCIPAL DISPLAY PANEL - 12 g Tube Carton

NDC 49035-178-08

equate™

Compare to Lotrimin Ultra®Jock Itch Active Ingredient*

CONTAINS THE DRUG:
BUTENAFINE HYDROCHLORIDE

Butenafine Hydrochloride Cream 1%
Antifungal

Clinically Proven To Cure Most Jock Itch

- Prescription Strength
- Relieves Itching, Burning and Chafing

NET WT
0.42 OZ (12 g)